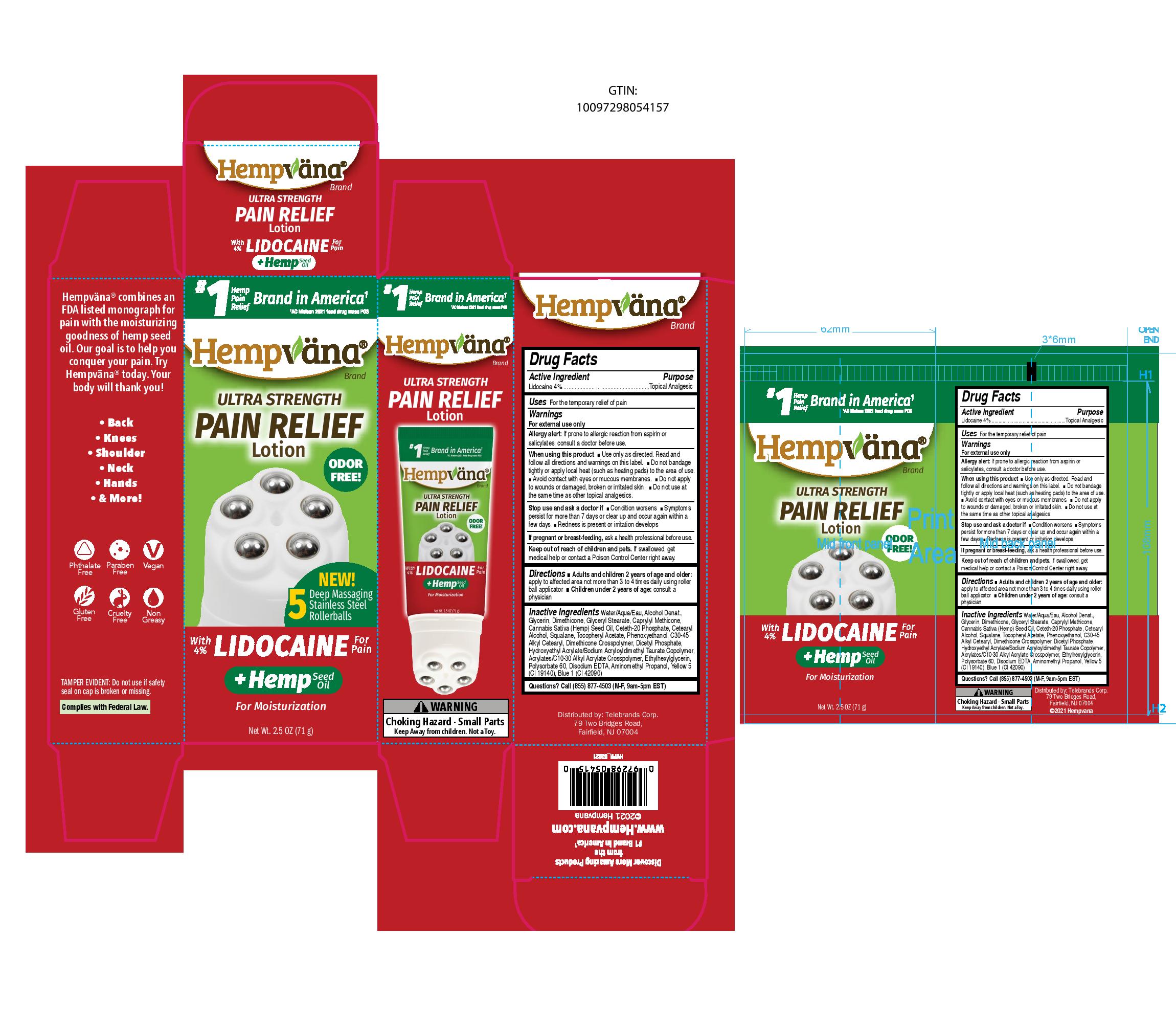 DRUG LABEL: Hempvana Ultra Strength Pain Relief
NDC: 73287-024 | Form: LOTION
Manufacturer: TELEBRANDS CORP
Category: otc | Type: HUMAN OTC DRUG LABEL
Date: 20241120

ACTIVE INGREDIENTS: LIDOCAINE 4 g/100 g
INACTIVE INGREDIENTS: ETHYLHEXYLGLYCERIN; POLYSORBATE 60; GLYCERIN; FD&C YELLOW NO. 5; WATER; DIHEXADECYL PHOSPHATE; HYDROXYETHYL ACRYLATE/SODIUM ACRYLOYLDIMETHYL TAURATE COPOLYMER (45000 MPA.S AT 1%); CARBOMER INTERPOLYMER TYPE A (ALLYL SUCROSE CROSSLINKED); EDETATE DISODIUM ANHYDROUS; DIMETHICONE; GLYCERYL MONOSTEARATE; ALCOHOL; .ALPHA.-TOCOPHEROL ACETATE; C30-45 ALKYL CETEARYL DIMETHICONE CROSSPOLYMER; AMINOMETHYLPROPANOL; FD&C BLUE NO. 1; CANNABIS SATIVA SEED OIL; CETETH-20 PHOSPHATE; SQUALANE; CETOSTEARYL ALCOHOL; PHENOXYETHANOL; CAPRYLYL TRISILOXANE

Hempvana Rollerballs (Lidocaine)

Active Ingredient

Lidocaine 4%

Purpose

Lidocaine 4%....................Topical Analgesic

Uses

For the temporary relief of pain

Warnings

For external use only

Allergy alert:If prone to allergic reaction from aspirin or salicylates, consult a doctor before use.

When using this product

- Use only as directed. Read and follow all directions and warnings on this label.
- Do not bandage tightly or apply local heat (such as heating pads) to the area of use.
- Avoid contact with eyes or mucous membranes.
- Do not apply to wounds or damaged, broken or irritated skin.
- Do not use at the same time as other topical analgesics.

Stop use and ask a doctor if

- Condition worsens
- Symptoms persist for more than 7 days or clear up and occur again within a few days
- Redness is present or irritation develops

PREGNANCY OR BREAST FEEDING

If pregnant or breast-feeding,ask a health professional before use.

Keep out of reach of children and pets.If swallowed, get medical help or contact a Poison Control Center right away.

Directions

- Adults and children 2 years of age and older:apply to affected area not more than 3 to 4 times daily using roller ball applicator
- Children under 2 years of age:consult a physician

Inactive Ingredients

Water/Aqua/Eau, Alcohol Denat., Glycerin, Dimethicone, Glyceryl Stearate, Caprylyl Methicone, Cannabis Sativa (Hemp) Seed Oil, Ceteth-20 Phosphate, Cetearyl Alcohol, Squalane, Tocopheryl Acetate, Phenoxyethanol, C30-45 Alkyl Cetearyl, Dimethicone Crosspolymer, Dicetyl Phosphate, Hydroxyethyl Acrylate/Sodium Acryloyldimethyl Taurate Copolymer, Acrylates/C10-30 Alkyl Acrylate Crosspolymer, Ethylhexylglycerin, Polysorbate 60, Disodium EDTA, Aminomethyl Propanol, Yellow 5 (CI 19140), Blue 1 (CI 42090)

Questions?

Call (855) 877-4503 (M-F, 9am-5pm EST)

PACKAGE LABEL

#1 Hemp Pain Relief Brand in America^1

^1AC Nielsen 2021 food drug mass POS

Hempvana Brand

Ultra Strength Pain Relief Lotion

Odor Free!

New! 5 Deep Massaging Stainless Steel Rollerballs

With 4% Lidocaine For Pain

+Hemp Seed Oil For Moisturization

Net Wt. 2.5 OZ (71 g)